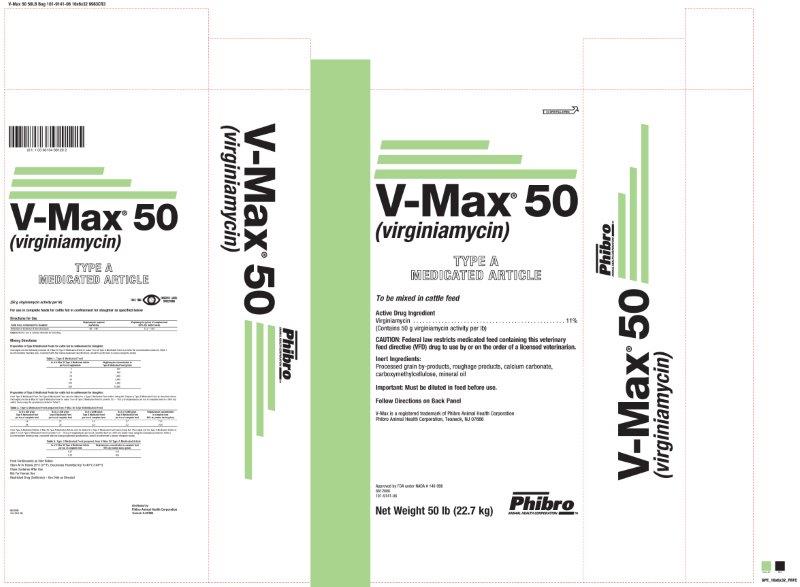 DRUG LABEL: V-Max 50
NDC: 66104-9601 | Form: POWDER
Manufacturer: Phibro Animal Health
Category: animal | Type: VFD TYPE A MEDICATED ARTICLE ANIMAL DRUG LABEL
Date: 20231107

ACTIVE INGREDIENTS: VIRGINIAMYCIN 227 g/0.45 kg
INACTIVE INGREDIENTS: CALCIUM CARBONATE; MINERAL OIL; CARBOXYMETHYLCELLULOSE SODIUM

V-MaxTM 50
(Virginiamycin)
TYPE A MEDICATED ARTICLE

DESCRIPTION

To be mixed in cattle feed

Active Drug Ingredient

Virginiamycin : 11%

(Contains 50 g virginiamycin activity per lb)

Caution

CAUTION: Federal law restricts medicated feed containing this veterinary feed directive (VFD) drug to use by or on the order of a licensed veterinarian.

Inert ingredients :

Processed grain by-products, roughage products, calcium carbonate, carboxymethylcellulose, mineral oil

INDICATIONS AND USAGE

Important: Must be diluted in feed before use

Follow Directions on Back Panel

V-Max is a registered trademark of Phibro Animal Health Corporation

Phibro Animal Health Corporation, Teaneck, NJ 07666

Approved by FDA under NADA # 140-998

8812000

101-9141-06

NET CONTENTS: 50 lb (22.7 kg)

Distributed by:

PHIBRO ANIMAL HEALTH, INC.

Teaneck, NJ 07666, USA

(50 g virginiamycin activity per lb) For use in complete feeds for cattle fed in confinement for slaughter as specified below Directions for Use

Cattle fed in confinement for slaughter | Virginiamycin required mg/hd/day | Virginiamycin (g/tons) of complete feed (90% dry matter basis)
Reduction of incidence of liver abscesse | 85–240 | 13.5–16.0
Caution: Not for use in animals intended for breeding.

Mixing Directions

Preparation ofType B Medicated Feeds for cattle fed in confinement for slaughter—Thoroughly mix the following amounts of V-Max 50 Type A Medicated Article to make 1 ton of Type B Medicated Feed to provide the concentrations shown in Table 1. An intermediate blending step, consistent with the mixing equipment specifications, should be performed to ensure adequate mixing.

Table 1. Type B Medicated Feed

lb of V-Max 50 Type A Medicated Article per ton of supplement | Virginiamycin concentration in Type B Medicated Feed (g/ton)
5; 10; 20; 40; 100; 200 | 250; 500; 1,000; 2,000; 5,000; 10,000

Preparation of Type C Medicated Feed for cattle fed in confinement for slaughter:

From Type B Medicated Feed: The Type B Medicated Feed must be diluted to a Type C Medicated Feed before being fed. Prepare a Type B Medicated Feed as described above. Thoroughly mix the V-Max 50 Type B Medicated Feed to make 1 ton of Type C Medicated Feed to provide 13.5 16.0 g of virginiamycin per ton of complete feed on a 90% dry matter basis using the examples provided in Table 2.

Table 2. Type C Medicated Feed prepared from V-Max 50 Type B Medicated Feed

lb of a 500g/ton Type B Medicated Feed per ton of complete feed | lb of a 1,000 g/ton Type B Medicated Feed per ton of complete feed | lb of a 5,000 g/ton Type B Medicated Feed per ton of complete feed | lb of a 10,000 g/ton Type B Medicated Feed per ton of complete feed | Virginiamycin concentration in complete feed 90% dry matter basis (g/ton)
54 | 27 | 5.4 | 2.7 | 13.5
64 | 32 | 6.4 | 3.2 | 16.0

From Type A Medicated Article: V-Max 50 Type A Medicated Article must be diluted to a Type C Medicated Feed before being fed. Thoroughly mix the Type A Medicated Article to make 1 ton of Type C Medicated Feed to provide 13.5 – 16.0 g of virginiamycin per ton of complete feed on a 90% dry matter basis using the examples provided in Table 3.

An intermediate blending step, consistent with the blending equipment specifications, should be performed to ensure adequate mixing.

Table 3. Type C Medicated Feed prepared from V-Max 50 Type A Medicated Article

lb of V-Max 50 Type A Medicated Article per ton of complete feed | Virginiamycin concentration in complete feed 90% dry matter basis (g/ton)
0.27; 0.32 | 13.5; 16.0

Feed continuously as sole ration

Store at or Below 25°C/77F°, Excursions Permitted Up To 40oC (104oF)

Close container after use

INDICATIONS AND USAGE

NOT FOR HUMAN USE

RESTRICTED DRUG (CALIFORNIA) – USE ONLY AS DIRECTED

V-Max 50 Label